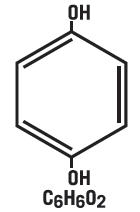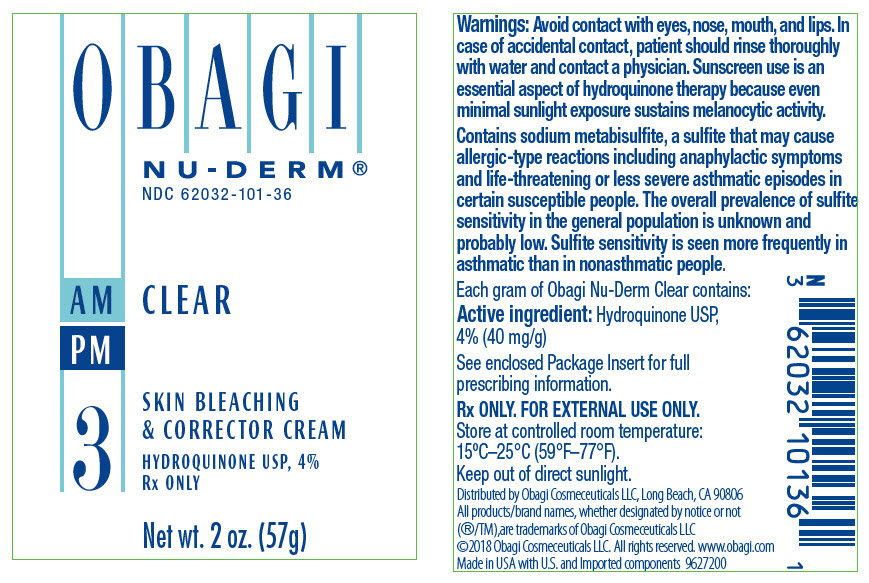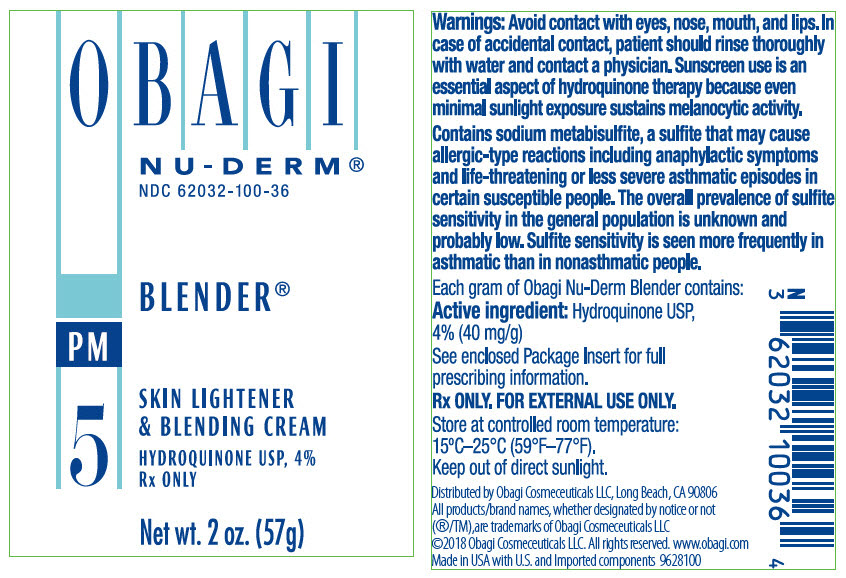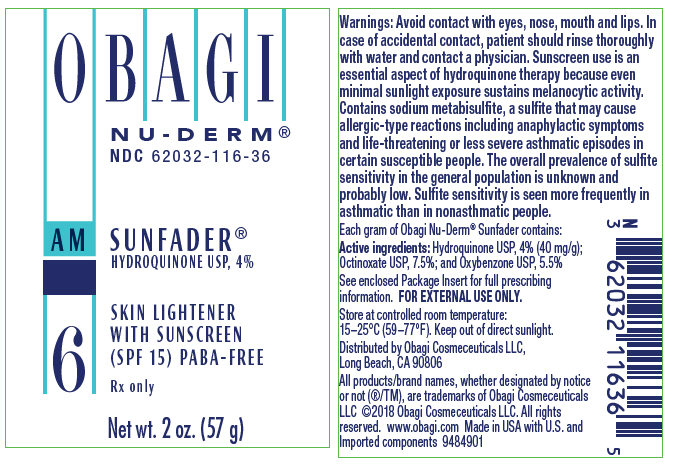 DRUG LABEL: NU-DERM CLEAR
NDC: 62032-101 | Form: CREAM
Manufacturer: Obagi Cosmeceuticals LLC
Category: prescription | Type: HUMAN PRESCRIPTION DRUG LABEL
Date: 20250101

ACTIVE INGREDIENTS: HYDROQUINONE 40 mg/1 g
INACTIVE INGREDIENTS: WATER; CETYL ALCOHOL; GLYCERIN; SODIUM LAURYL SULFATE; STEARYL ALCOHOL; LACTIC ACID, UNSPECIFIED FORM; .ALPHA.-TOCOPHEROL ACETATE; ASCORBIC ACID; SODIUM METABISULFITE; EDETATE DISODIUM; METHYLPARABEN; BUTYLATED HYDROXYTOLUENE; PROPYLPARABEN; BUTYLPARABEN

Obagi Nu-Derm® Clear
(Hydroquinone USP, 4%) Skin Bleaching Cream
Obagi Nu-Derm Blender®
(Hydroquinone USP, 4%)
Skin Bleaching Cream
Obagi Nu-Derm Sunfader®
(Hydroquinone USP, 4%; Octinoxate USP, 7.5%;
Oxybenzone USP, 5.5%)
Skin Bleaching Cream with Sunscreens

Rx Only

For external use only

DESCRIPTION

Hydroquinone is 1, 4-benzenediol. The drug is freely soluble in water and in alcohol. Chemically, hydroquinone is designed as p-dihydroxybenzene; the empirical formula is C6H6O2; molecular weight is 110.11 g/mol. The chemical structure is in the diagram below.

Each gram of Obagi Nu-Derm Clear contains:

Active ingredient: Hydroquinone USP, 4% (40 mg/g)

Inactive ingredients: water, cetyl alcohol, glycerin, sodium lauryl sulfate, stearyl alcohol, lactic acid, tocopheryl acetate, ascorbic acid, sodium metabisulfite, disodium EDTA, methylparaben, BHT, propylparaben, saponins, butylparaben

Each gram of Obagi Nu-Derm Blender contains:

Active ingredient: Hydroquinone USP, 4% (40 mg/g)

Inactive ingredients: water, glycerin, cetyl alcohol, PPG-2 myristyl ether propionate, sodium lauryl sulfate, TEA-salicylate, lactic acid, phenyl trimethicone, tocopheryl acetate, sodium metabisulfite, ascorbic acid, methylparaben, disodium EDTA, propylparaben, saponins, BHT

Each gram of Obagi Nu-Derm Sunfader contains:

Active ingredients: Hydroquinone USP, 4% (40 mg/g); Octinoxate USP, 7.5%; Oxybenzone USP, 5.5%

Inactive ingredients: water, cetyl alcohol, glycerin, sodium lauryl sulfate, stearyl alcohol, tocopheryl acetate, ascorbic acid, sodium metabisulfite, disodium EDTA, methylparaben, BHT, saponins, propylparaben, butylparaben

CLINICAL PHARMACOLOGY

Topical application of hydroquinone produces a reversible depigmentation of the skin by inhibition of the enzymatic oxidation of tyrosine to 3, 4-dihydroxyphenylalanine (DOPA) and suppression of other melanocyte metabolic processes. Exposure to sunlight or ultraviolet light will cause repigmentation of the bleached areas, which may be prevented by the use of sunblocking agents or sunscreen agents contained in Obagi Nu-Derm Sunfader and Obagi Nu-Derm Sun Shield Matte Broad Spectrum SPF 50.

INDICATIONS AND USAGE

For the gradual bleaching of hyperpigmented skin conditions such as chloasma, melasma, freckles, senile lentigines, and other unwanted areas of melanin hyperpigmentation.

CONTRAINDICATIONS

People with prior history of sensitivity or allergic reaction to this product or any of its ingredients should not use it. The safety of topical hydroquinone use during pregnancy or in children (12 years and under) has not been established.

WARNINGS

Hydroquinone is a skin-bleaching agent, which may produce unwanted cosmetic effects if not used as directed. The physician should be familiar with the contents of this insert before prescribing or dispensing this product.

Test for skin sensitivity before using by applying a small amount to an unbroken patch of skin and check within 24 hours. Minor redness is not a contraindication, but where there is itching or vesicle formation or excessive inflammatory response, product should be discontinued and physician consulted. Close patient supervision is recommended.

Warnings: Avoid contact with eyes, nose, mouth, and lips.In case of accidental contact, patient should rinse thoroughly with water and contact a physician. Sunscreen use is an essential aspect of hydroquinone therapy because even minimal sunlight exposure sustains melanocytic activity.

Contains sodium metabisulfite, a sulfite that may cause allergic-type reactions including anaphylactic symptoms and life-threatening or less severe asthmatic episodes in certain susceptible people. The overall prevalence of sulfite sensitivity in the general population is unknown and probably low. Sulfite sensitivity is seen more frequently in asthmatic than in nonasthmatic people.

PRECAUTIONS

(Also see WARNINGS)

Treatment should be limited to relatively small areas of the body at one time since some patients experience a transient skin reddening and a mild burning sensation, which does not preclude treatment.

Pregnancy Category C

Animal reproduction studies have not been conducted with topical hydroquinone. It is also not known whether hydroquinone can cause fetal harm when used topically on a pregnant woman or affect reproductive capacity. It is not known to what degree, if any, topical hydroquinone is absorbed systemically. Topical hydroquinone should be used on pregnant women only when clearly indicated.

Nursing Mothers

It is not known whether topical hydroquinone is absorbed or excreted in human milk. Caution is advised when topical hydroquinone is used by a nursing mother.

Pediatric Usage

Safety and effectiveness in children below the age of 12 years have not been established.

ADVERSE REACTIONS

No systemic adverse reactions have been reported. Occasional hypersensitivity (localized contact dermatitis) may occur, in which case the product should be discontinued and the physician notified immediately.

DOSAGE AND ADMINISTRATION

A thin application should be applied once or twice daily or as directed by a physician. If no improvement is seen after three (3) months of treatment, use of this product should be discontinued. Sun exposure should be limited by using a sunscreen agent, a sunblocking agent, or protective clothing to cover bleached skin when using and after using this product in order to prevent darkening from reoccurring.

HOW SUPPLIED

Obagi Nu-Derm Clear is available as follows:

Net wt. 2 oz. (57 g) bottle
NDC 62032-101-36

Obagi Nu-Derm Blender is available as follows:

Net wt. 2 oz. (57 g) bottle
NDC 62032-100-36

Net wt. 1 oz. (28 g) bottle
NDC 62032-100-10

Obagi Nu-Derm Sunfader is available as follows:

Net wt. 2 oz. (57 g) bottle
NDC 62032-116-36

STORAGE AND HANDLING

Store at controlled room temperature: 15°C-25°C (59°F-77°F). Keep out of direct sunlight.

⍰ 1-800-636-7546

Manufactured for:
Obagi Cosmeceuticals LLC,
Long Beach, CA 90806

All products/brand names, whether designated by notice or not (®/TM), are trademarks of Obagi Cosmeceuticals LLC

©2018 Obagi Cosmeceuticals LLC.
All rights reserved.
www.obagi.com

Revised 03/2018
9458403

PRINCIPAL DISPLAY PANEL - 57 g Bottle Label - 3

OBAGI

NU-DERM®
NDC 62032-101-36

AM CLEAR
PM
3

SKIN BLEACHING
& CORRECTOR CREAM

HYDROQUINONE USP, 4%
Rx ONLY

Net wt. 2 oz. (57g)

PRINCIPAL DISPLAY PANEL - 57 g Bottle Label - 5

OBAGI

NU-DERM®
NDC 62032-100-36

BLENDER®

PM
5

SKIN LIGHTENER
& BLENDING CREAM

HYDROQUINONE USP, 4%
Rx ONLY

Net wt. 2 oz. (57g)

PRINCIPAL DISPLAY PANEL - 57 g Bottle Label - 6

OBAGI

NU-DERM®
NDC 62032-116-36

AM
6

SUNFADER®
HYDROQUINONE USP, 4%

SKIN LIGHTENER
WITH SUNSCREEN
(SPF 15) PABA-FREE

Rx only

Net wt. 2 oz. (57 g)